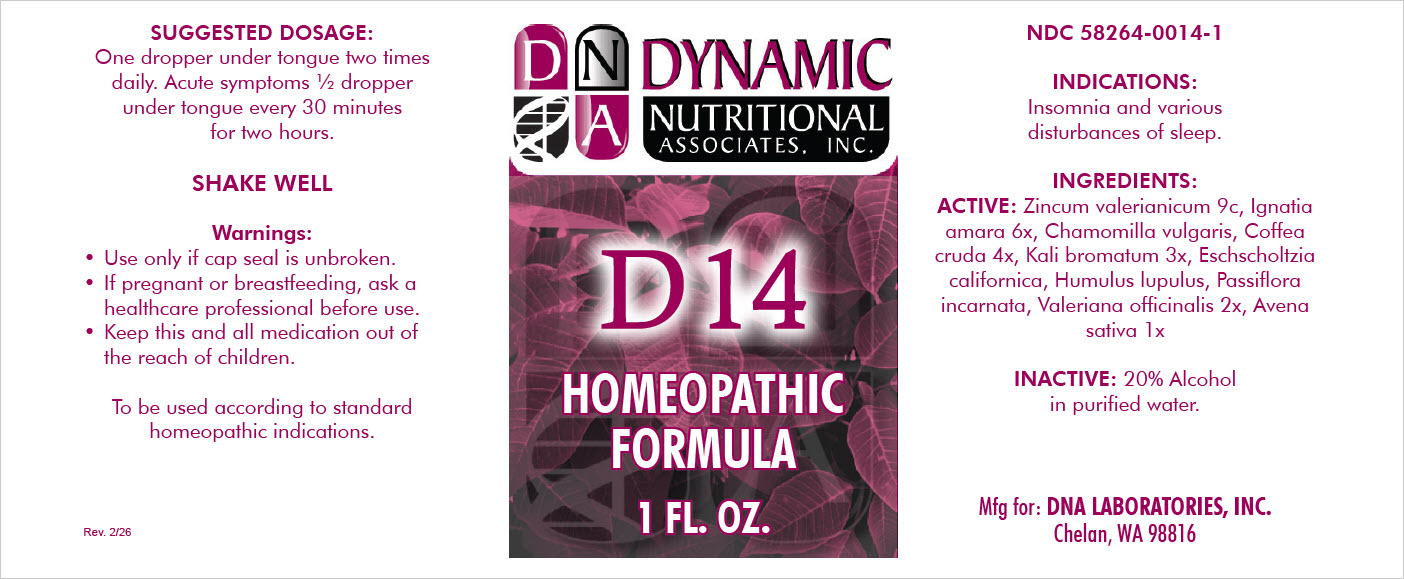 DRUG LABEL: D14
NDC: 58264-1014 | Form: SOLUTION
Manufacturer: DNA Labs, Inc.
Category: homeopathic | Type: HUMAN OTC DRUG LABEL
Date: 20260225

ACTIVE INGREDIENTS: AVENA SATIVA WHOLE 1 [hp_X]/1 mL; VALERIANA OFFICINALIS WHOLE 1 [hp_X]/1 mL; HUMULUS LUPULUS WHOLE 2 [hp_X]/1 mL; ARABICA COFFEE BEAN 4 [hp_X]/1 mL; STRYCHNOS IGNATII WHOLE 6 [hp_X]/1 mL; ZINC VALERATE DIHYDRATE 9 [hp_X]/1 mL; CHAMOMILE 4 [hp_X]/1 mL; ESCHSCHOLZIA CALIFORNICA 2 [hp_X]/1 mL; PASSIFLORA INCARNATA WHOLE 2 [hp_X]/1 mL; POTASSIUM BROMIDE 3 [hp_X]/1 mL
INACTIVE INGREDIENTS: ALCOHOL; WATER

D-14

NDC 58264-0014-2

INDICATIONS AND USAGE

INDICATIONS

Insomnia and various disturbances of sleep.

ACTIVE INGREDIENT

Zincum valerianicum 9c, Ignatia amara 6x, Chamomilla vulgaris, Coffea cruda 4x, Kali bromatum 3x, Eschscholtzia californica, Humulus lupulus, Passiflora incarnata, Valeriana officinalis 2x, Avena sativa 1x

INGREDIENTS

20% alcohol in purified water.

SUGGESTED DOSAGE

One dropper full under the tongue two times daily. In acute conditions 5-10 drops under the tongue every 20-30 minutes.

STORAGE AND HANDLING

SHAKE WELL

Warnings

- Use only if cap seal is unbroken.

PREGNANCY OR BREAST FEEDING

- As with drugs if you are pregnant or nursing a baby seek professional advice before using this product.

KEEP OUT OF REACH OF CHILDREN

- Keep this and all medication out of the reach of children.

To be used according to standard homeopathic indications.

PRINCIPAL DISPLAY PANEL - 1 FL. OZ. Bottle Label

DYNAMIC
NUTRITIONAL
ASSOCIATES, INC.

D 14

HOMEOPATHIC FORMULA

1 FL. OZ.